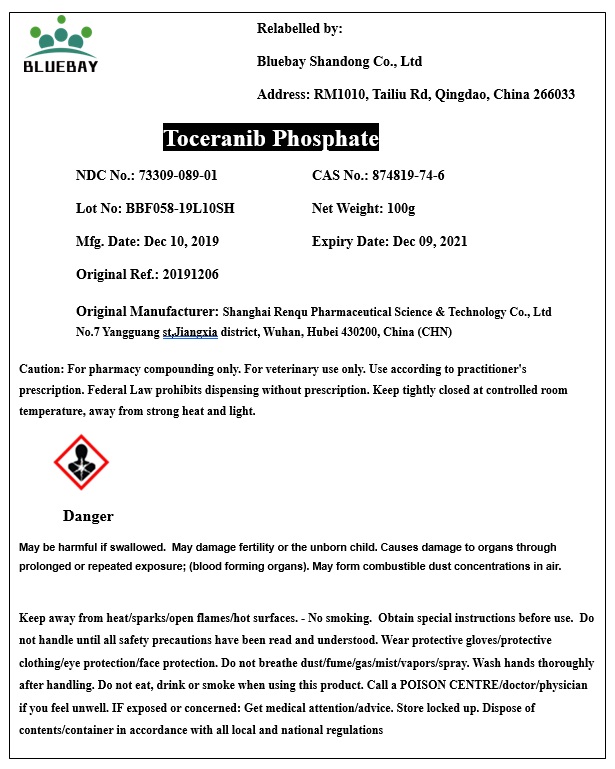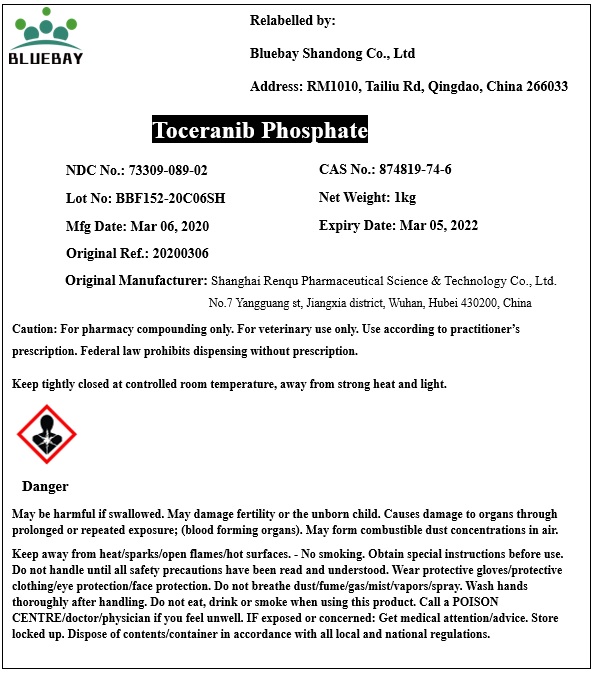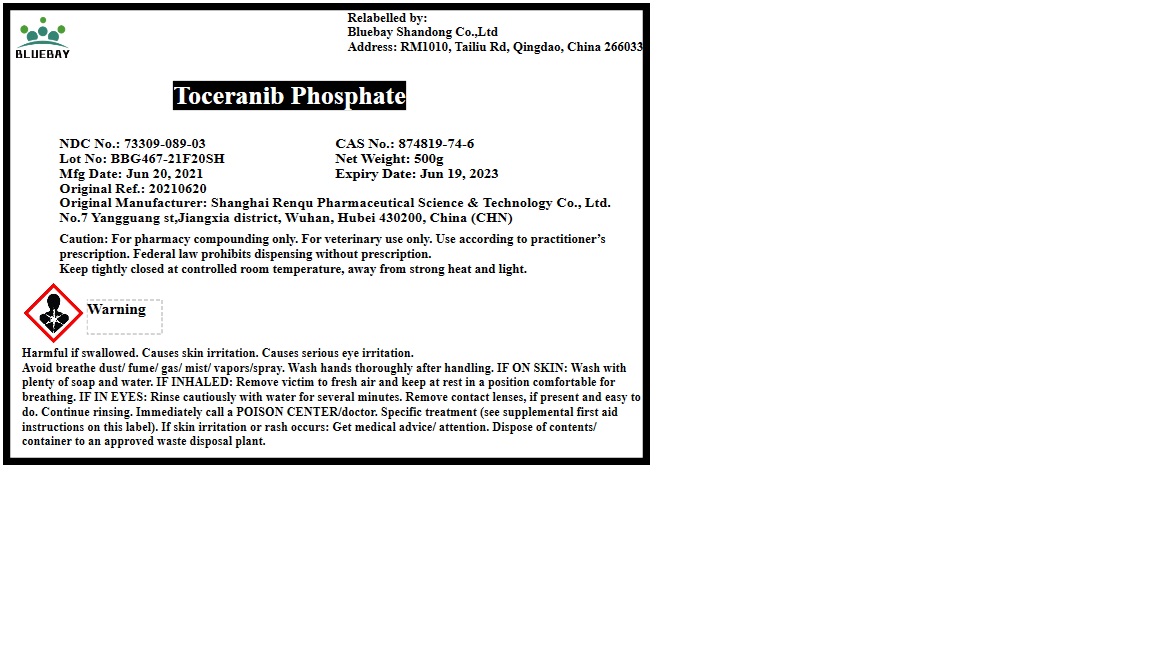 DRUG LABEL: Toceranib Phosphate
NDC: 73309-089 | Form: POWDER
Manufacturer: BLUEBAY SHANDONG CO.,LTD
Category: other | Type: BULK INGREDIENT
Date: 20210922

ACTIVE INGREDIENTS: Toceranib Phosphate 1 g/1 g

Toceranib Phosphate